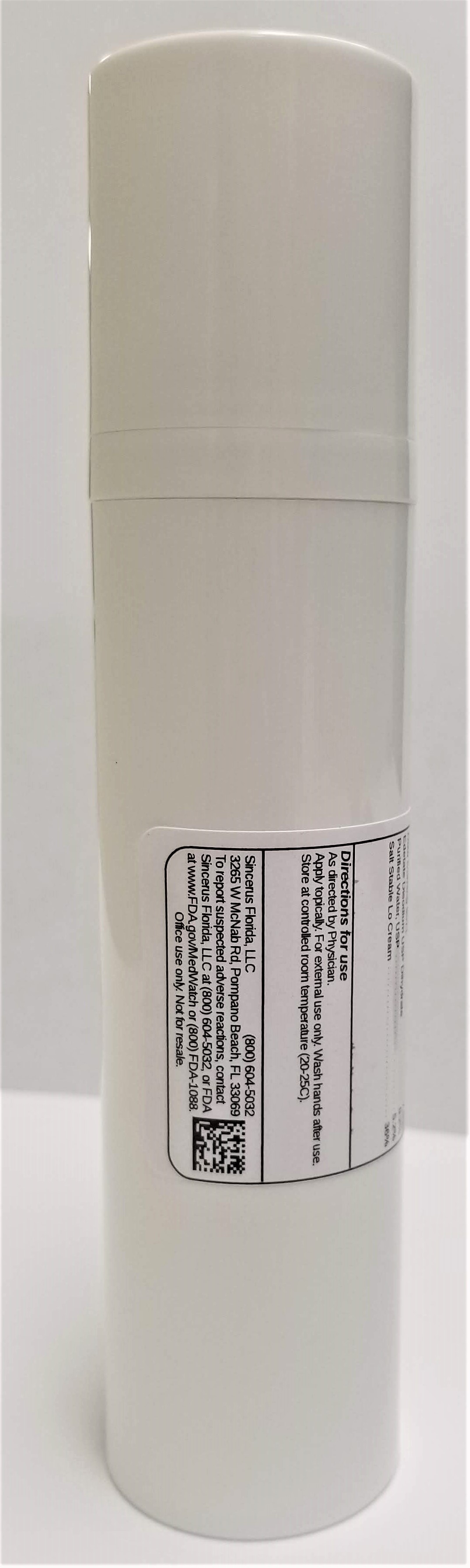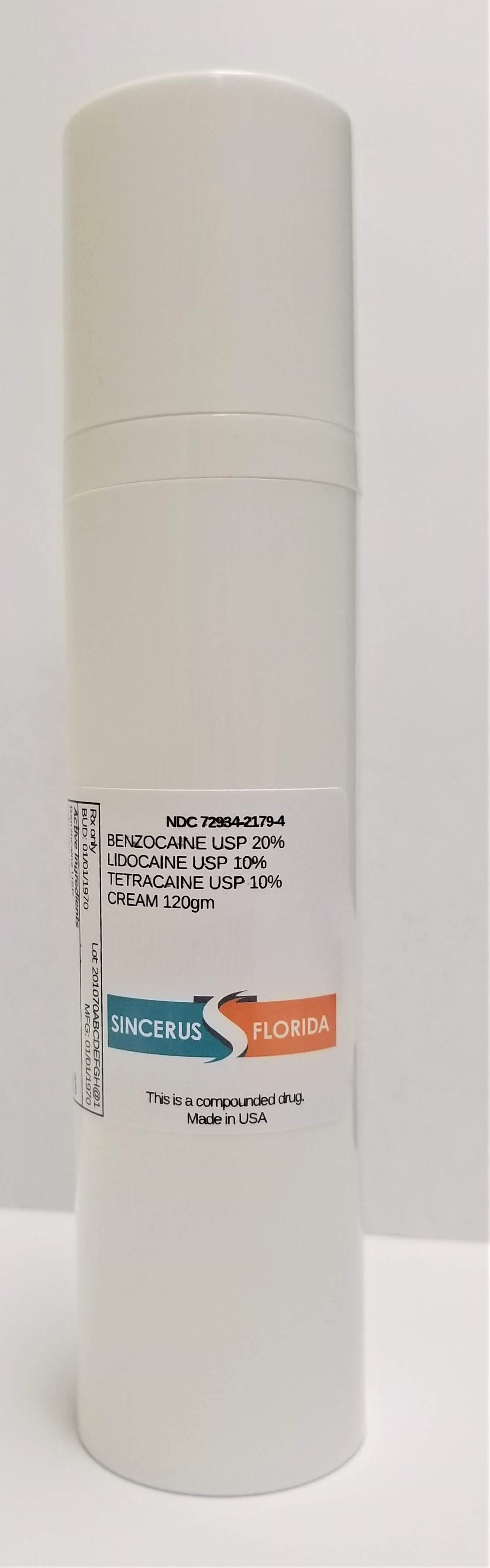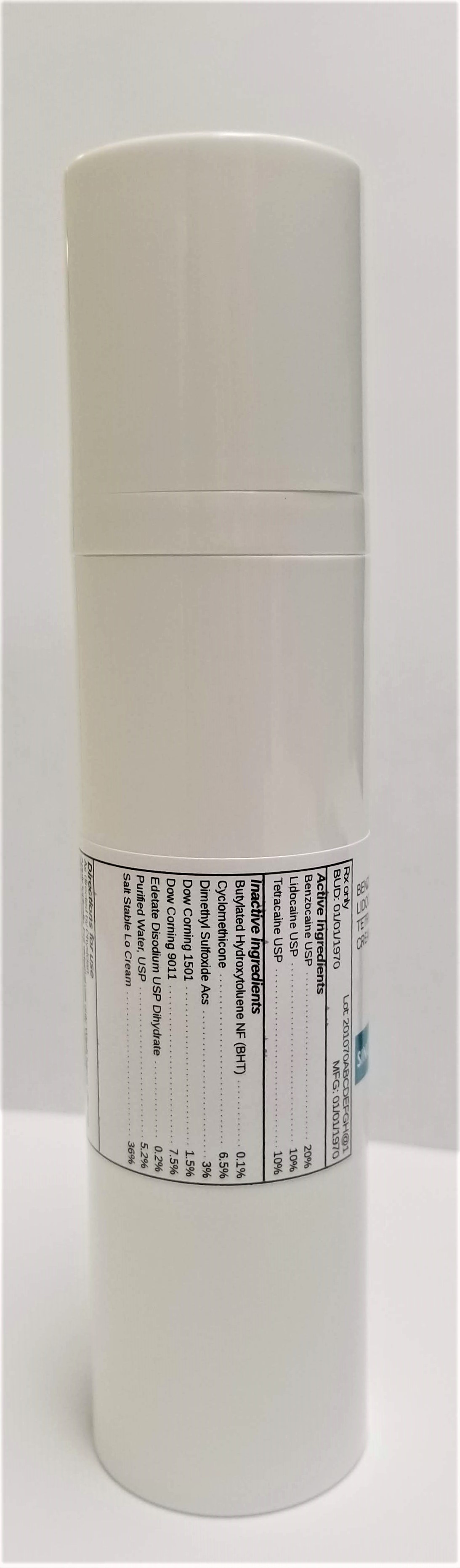 DRUG LABEL: BENZOCAINE 20% / LIDOCAINE 10% / TETRACAINE 10%
NDC: 72934-2179 | Form: CREAM
Manufacturer: Sincerus Florida, LLC
Category: prescription | Type: HUMAN PRESCRIPTION DRUG LABEL
Date: 20190522

ACTIVE INGREDIENTS: LIDOCAINE 10 g/100 g; BENZOCAINE 20 g/100 g; TETRACAINE 10 g/100 g

BENZOCAINE 20% / LIDOCAINE 10% / TETRACAINE 10%